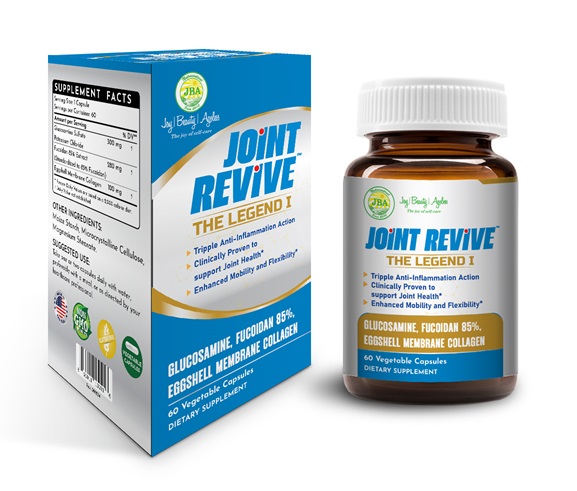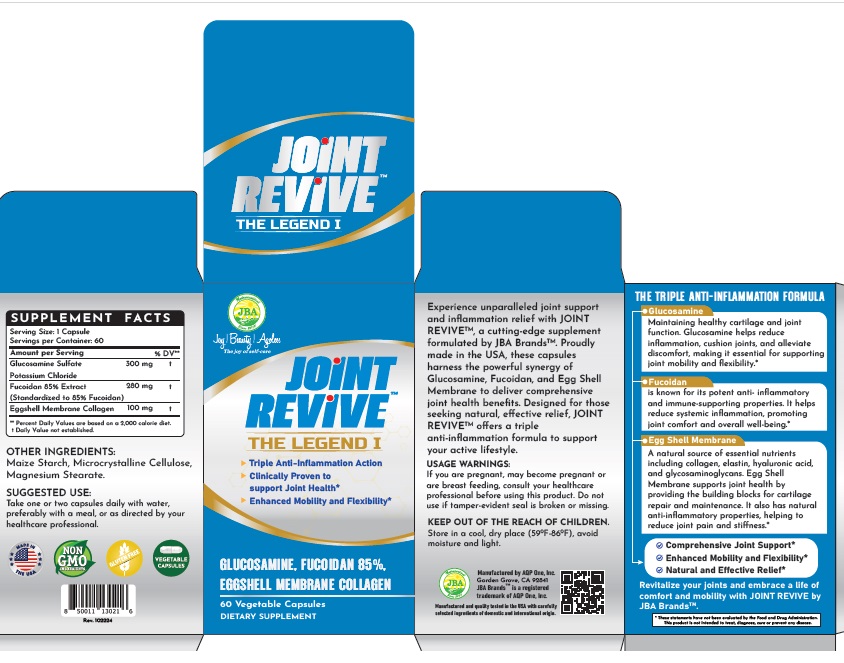 DRUG LABEL: JBA Joint Revive The Legend I
NDC: 13411-859 | Form: CAPSULE
Manufacturer: Advanced Pharmaceutical Services, Inc. Dba Affordable Quality Pharmaceuticals
Category: otc | Type: HUMAN OTC DRUG LABEL
Date: 20251128

ACTIVE INGREDIENTS: LAMINARIA JAPONICA 280 mg/1 1; EGG SHELL MEMBRANE 100 mg/1 1; GLUCOSAMINE SULFATE POTASSIUM CHLORIDE 300 mg/1 1
INACTIVE INGREDIENTS: STARCH, CORN; MICROCRYSTALLINE CELLULOSE; MAGNESIUM STEARATE

Identity

Dietary supplement

Direction

Take one or two capsules daily with water, preferably with a meal, or as directed by your healthcare professional.

Safe handling warning

JOINT REVIVE™ THE LEGEND I
- Triple Anti-Inflammation Action*
- Clinically Proven to Support Joint Health*
- Enhanced Mobility and Flexibility*

Experience unparalleled joint support and inflammation relief with JOINT REVIVE™, a cutting-edge supplement formulated by JBA Brands™. Proudly made in the USA, these capsules harness the powerful synergy of Glucosamine, Fucoidan, and Egg Shell Membrane to deliver comprehensive joint health benefits. Designed for those seeking natural, effective relief, JOINT REVIVE™ offers a triple anti-inflammation formula to support your active lifestyle.

THE TRIPLE ANTI-INFLAMMATION FORMULA

Glucosamine

Maintaining healthy cartilage and joint function. Glucosamine helps reduce inflammation, cushion joints, and alleviate discomfort, making it essential for supporting joint mobility and flexibility .*

Fucoidan

is known for its potent anti- inflammatory and immune-supporting properties. It helps reduce systemic inflammation, promoting joint comfort and overall well-being .*

Egg Shell Membrane
A natural source of essential nutrients including collagen, elastin, hyaluronic acid, and glycosaminoglycans. Egg Shell Membrane supports joint health by providing the building blocks for cartilage repair and maintenance. It also has natural anti-inflammatory properties, helping to reduce joint pain and stiffness .*

- Comprehensive Joint Support*
- Enhanced Mobility and Flexibility*
- Natural and Effective Relief*

Revitalize your joints and embrace a life of comfort and mobility with JOINT REVIVE by JBA Brands™.

* These statements have not been evaluated by the Food & Drug Administration. This product is not intended to diagnose, treat, cure, or prevent any disease.

PRECAUTIONS

If you are pregnant, may become pregnant or are breast feeding, consult your healthcare professional before using this product. Do not use if tamper-evident seal is broken or missing.

Keep Out of The Reach of Children.

Store in a cool, dry place (59oF-86oF), avoid moisture and light.

WARNINGS

Other Ingredients

Maize Starch, Microcrystalline Cellulose, Magnesium Stearate